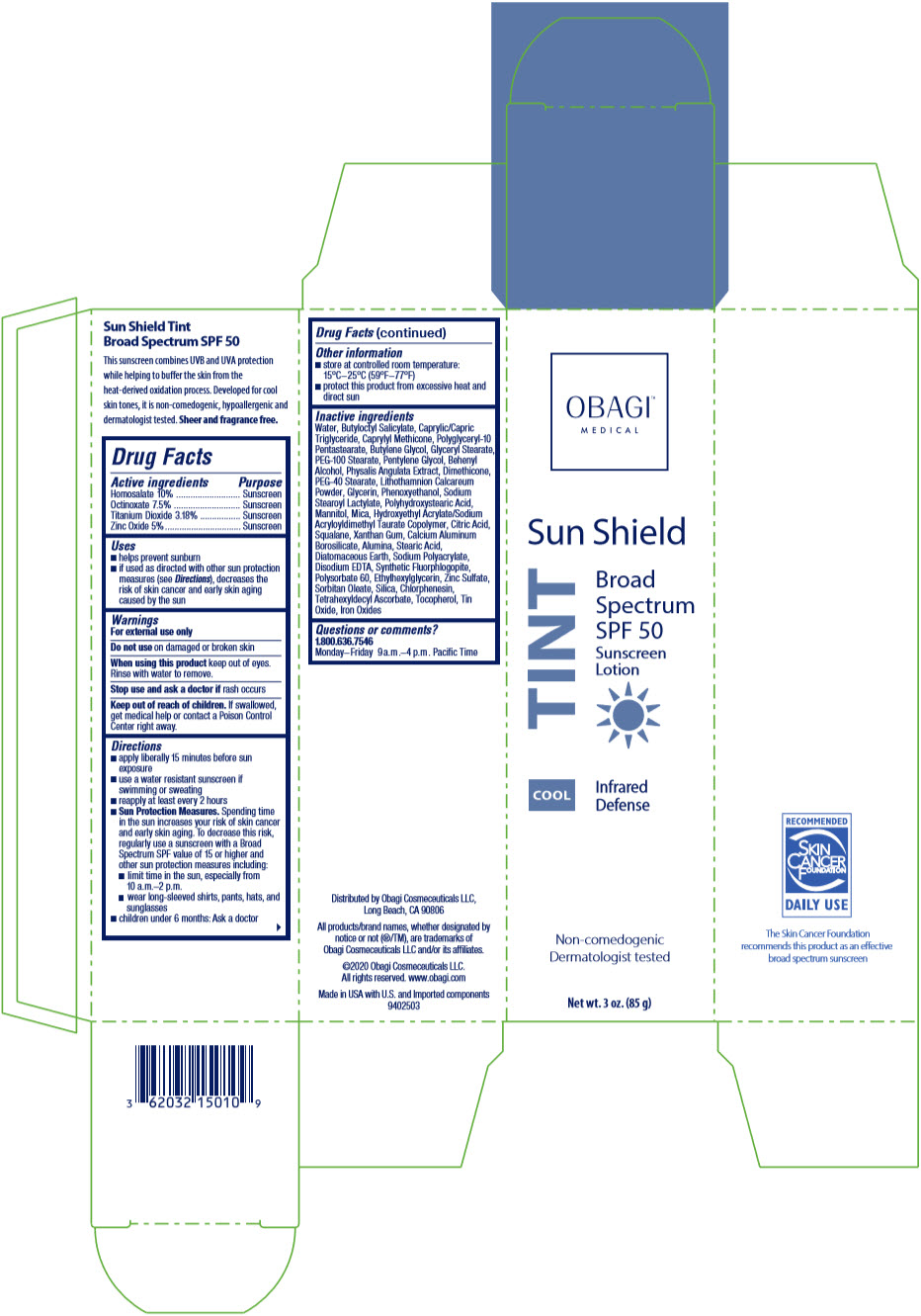 DRUG LABEL: Obagi
NDC: 62032-150 | Form: LOTION
Manufacturer: Obagi Cosmeceuticals LLC
Category: otc | Type: HUMAN OTC DRUG LABEL
Date: 20210211

ACTIVE INGREDIENTS: HOMOSALATE 8.5 g/85 g; OCTINOXATE 6.375 g/85 g; TITANIUM DIOXIDE 2.703 g/85 g; ZINC OXIDE 4.25 g/85 g
INACTIVE INGREDIENTS: WATER; BUTYLOCTYL SALICYLATE; MEDIUM-CHAIN TRIGLYCERIDES; CAPRYLYL TRISILOXANE; 12-OXOOCTADECANOIC ACID; GLYCERYL MONOSTEARATE; PEG-100 STEARATE; BUTYLENE GLYCOL; PENTYLENE GLYCOL; DOCOSANOL; EDETATE DISODIUM ANHYDROUS; PEG-40 STEARATE; DIMETHICONE; PHYSALIS ANGULATA WHOLE; POLYGLYCERYL-10 PENTASTEARATE; FUCUS VESICULOSUS; GLYCERIN; FERRIC OXIDE RED; PHENOXYETHANOL; PHYMATOLITHON CALCAREUM; SODIUM STEAROYL LACTYLATE; SORBITAN MONOOLEATE; POLYHYDROXYSTEARIC ACID (2300 MW); MANNITOL; MICA; HYDROXYETHYL ACRYLATE/SODIUM ACRYLOYLDIMETHYL TAURATE COPOLYMER (100000 MPA.S AT 1.5%); CITRIC ACID MONOHYDRATE; SQUALANE; ALUMINUM OXIDE; STEARIC ACID; MAGNESIUM POTASSIUM ALUMINOSILICATE FLUORIDE; XANTHAN GUM; ZINC SULFATE MONOHYDRATE; CALCIUM ALUMINUM BOROSILICATE; DIATOMACEOUS EARTH; SODIUM POLYACRYLATE (2500000 MW); EDETATE DISODIUM; POLYSORBATE 60; ETHYLHEXYLGLYCERIN; FERROUS OXIDE; ZINC SULFATE, UNSPECIFIED FORM; SILICON DIOXIDE; CHLORPHENESIN; TETRAHEXYLDECYL ASCORBATE; STANNIC OXIDE; TOCOPHEROL

OBAGI®
Sun Shield TINT Cool Sunscreen
Broad Spectrum SPF 50

Drug Facts

ACTIVE INGREDIENT

Active ingredients | Purpose
Homosalate 10%; Octinoxate 7.5%; Titanium dioxide 3.18% | Sunscreen; Sunscreen; Sunscreen
Zinc oxide 5% | Sunscreen

Uses

- helps prevent sunburn
- if used as directed with other sun protection measures (see Directions), decreases the risk of skin cancer and early skin aging caused by the sun

Warnings

- For external use only
- Do not use on damaged or broken skin
- When using this product keep out of eyes. Rinse with water to remove.
- Stop use and ask a doctor if rash occurs
- Keep out of reach of children. If swallowed, get medical help or contact a Poison Control Center right away.

Directions

- apply liberally 15 minutes before sun exposure
- use a water resistant sunscreen if swimming or sweating
- reapply at least every 2 hours
- children under 6 months: Ask a doctor
- Sun Protection Measures. Spending time in the sun increases your risk of skin cancer and early skin aging. To decrease this risk, regularly use a sunscreen with a Broad Spectrum SPF value of 15 or higher and other sun protection measures including:
  - limit time in the sun, especially from 10 a.m.-2 p.m.
  - wear long-sleeved shirts, pants, hats and sunglasses

Other information

- store at controlled room temperature: 15°C–25°C (59°F–77°F)
- protect this product from excessive heat and direct sun

Inactive ingredients

water, butyloctyl salicylate, caprylic/capric triglyceride, caprylyl methicone, polyglyceryl-10 pentastearate, glyceryl stearate, PEG-100 stearate, butylene glycol, pentylene glycol, behenyl alcohol, PEG-40 stearate, dimethicone, physalis angulata extract, algae extract, glycerin, iron oxides, phenoxyethanol, sodium stearoyl lactylate, polyhydroxystearic acid, mannitol, mica, hydroxyethyl acrylate/sodium acryloyldimethyl taurate copolymer, citric acid, squalane, alumina, stearic acid, xanthan gum, calcium aluminium borosilicate, diatomaceous earth, Sodium Polyacrylate, disodium EDTA, synthetic fluorphlogopite, polysorbate 60, ethylhexylglycerin, zinc sulfate, Sorbitan Oleate, silica, chlorphenesin, tetrahexyldecyl ascorbate, tin oxide, tocopherol

Questions or comments?

1.800.636.7546

Monday–Friday 9 a.m.–4 p.m. Pacific Time

Distributed by Obagi Cosmeceuticals LLC,
Long Beach, CA 90806

PRINCIPAL DISPLAY PANEL - 85 g Tube Carton

OBAGI™
MEDICAL

Sun Shield

TINT

COOL

Broad
Spectrum
SPF 50
Sunscreen
Lotion

Infrared
Defense

Non-comedogenic
Dermatologist tested

Net wt. 3 oz. (85 g)